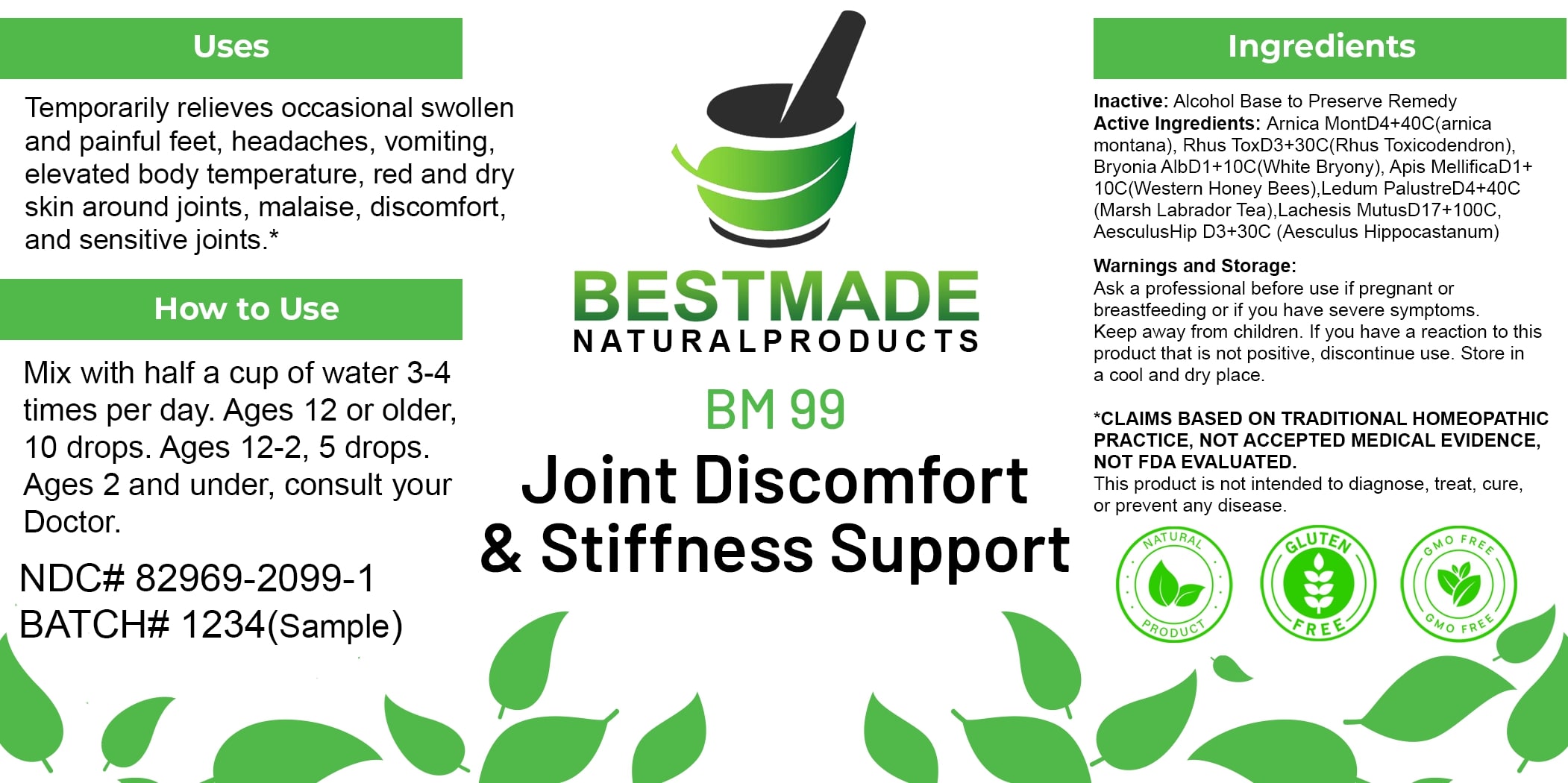 DRUG LABEL: Bestmade Natural Products BM99
NDC: 82969-2099 | Form: LIQUID
Manufacturer: Bestmade Natural Products
Category: homeopathic | Type: HUMAN OTC DRUG LABEL
Date: 20250206

ACTIVE INGREDIENTS: ARNICA MONTANA 30 [hp_C]/30 [hp_C]; LEDUM PALUSTRE TWIG 30 [hp_C]/30 [hp_C]; LACHESIS MUTA VENOM 30 [hp_C]/30 [hp_C]; BRYONIA ALBA ROOT 30 [hp_C]/30 [hp_C]; APIS MELLIFERA 30 [hp_C]/30 [hp_C]; TOXICODENDRON PUBESCENS LEAF 30 [hp_C]/30 [hp_C]; HORSE CHESTNUT 30 [hp_C]/30 [hp_C]
INACTIVE INGREDIENTS: ALCOHOL 30 [hp_C]/30 [hp_C]

BM99

DOSAGE AND ADMINISTRATION

How to Use

Mix with half a cup of water 3-4 times per day. Ages 12 or older, 10 drops. Ages 12-2, 5 drops. Ages 2 and under, consult your Doctor.

INACTIVE INGREDIENT

Ingredients

Inactive: Alcohol Base to Preserve Remedy

ACTIVE INGREDIENT

Active Ingredients: Arnica Mont D4+40C (Arnica montana), Rhus Tox D3+30C (Rhus Toxicodendron), Bryonia Alb D1+10C (White Bryony), Apis Mellifica D1+10C (Western Honey Bees) Ledum Palustre D4+40C (Marsh Labrador Tea), Lachesis Mutus D17+100C, Aesculus Hip D3+30C (Aesculus Hippocastanum)

Uses

Temporarily relieves occasional swollen and painful feet, headaches, vomiting, elevated body temperature, red and dry skin around joints, malaise, discomfort, and sensitive joints.*

*CLAIMS BASED ON TRADITIONAL HOMEOPATHIC PRACTICE, NOT ACCEPTED MEDICAL EVIDENCE, NOT FDA EVALUATED.

This product is not intended to diagnose, treat, cure, or prevent any disease.

Uses

Temporarily relieves occasional swollen and painful feet, headaches, vomiting, elevated body temperature, red and dry skin around joints, malaise, discomfort, and sensitive joints.*

*CLAIMS BASED ON TRADITIONAL HOMEOPATHIC PRACTICE, NOT ACCEPTED MEDICAL EVIDENCE, NOT FDA EVALUATED.

This product is not intended to diagnose, treat, cure, or prevent any disease.

KEEP OUT OF REACH OF CHILDREN

Warnings and Storage:

Ask a professional before use if pregnant or breastfeeding or if you have severe symptoms. Keep away from children. If you have a reaction to this product that is not positive, discontinue use. Store in a cool and dry place.

Warnings and Storage:

Ask a professional before use if pregnant or breastfeeding or if you have severe symptoms. Keep away from children. If you have a reaction to this product that is not positive, discontinue use. Store in a cool and dry place.

*CLAIMS BASED ON TRADITIONAL HOMEOPATHIC PRACTICE, NOT ACCEPTED MEDICAL EVIDENCE, NOT FDA EVALUATED.

This product is not intended to diagnose, treat, cure, or prevent any disease.

Entire package label